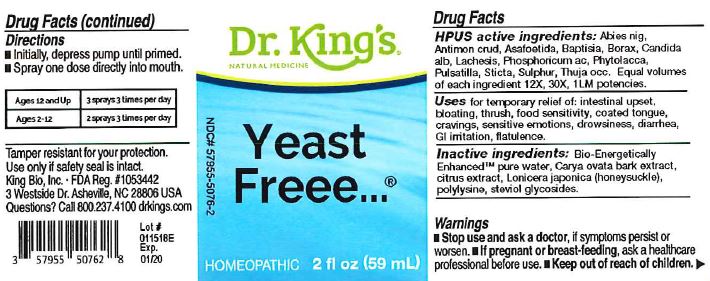 DRUG LABEL: Yeast Freee
NDC: 57955-5076 | Form: LIQUID
Manufacturer: King Bio Inc.
Category: homeopathic | Type: HUMAN OTC DRUG LABEL
Date: 20180222

ACTIVE INGREDIENTS: PICEA MARIANA RESIN 12 [hp_X]/59 mL; ANTIMONY TRISULFIDE 12 [hp_X]/59 mL; ASAFETIDA 12 [hp_X]/59 mL; BAPTISIA TINCTORIA ROOT 12 [hp_X]/59 mL; SODIUM BORATE 12 [hp_X]/59 mL; CANDIDA ALBICANS 12 [hp_X]/59 mL; LACHESIS MUTA VENOM 12 [hp_X]/59 mL; PHOSPHORIC ACID 12 [hp_X]/59 mL; PHYTOLACCA AMERICANA ROOT 12 [hp_X]/59 mL; PULSATILLA VULGARIS 12 [hp_X]/59 mL; LOBARIA PULMONARIA 12 [hp_X]/59 mL; SULFUR 12 [hp_X]/59 mL; THUJA OCCIDENTALIS LEAFY TWIG 12 [hp_X]/59 mL
INACTIVE INGREDIENTS: WATER; CARYA OVATA BARK; CITRUS BIOFLAVONOIDS; LONICERA JAPONICA FLOWER; POLYEPSILON-LYSINE (4000 MW); REBAUDIOSIDE A

Yeast Freee....

ACTIVE INGREDIENT

Drug Facts__________________________________________________________________________________________________________

HPUS active ingredients: Abies nig, Antimonium crud, Asafoetida, Baptisia, Borax, Candida alb, Lachesis, Phosphoricum ac, Phytolacca, Pulsatilla, Sticta, Sulphur, Thuja occ.

Equal volumes of each ingredient in 12X, 30X, 1LM potencies.

INDICATIONS AND USAGE

Uses for temporary relief of: intestinal upset, bloating, thrush, food sensitivity, coated tongue, cravings, sensitive emotions, drowsiness, diarrhea, GI iritation, flatulence.

Inactive Ingredients:

Bio-Energetically Enhanced™ pure water, Carya ovata bak extract, citrus extract, Lonicera japonica (honeysuckle), polylysine, steviol glycosides.

Warnings

- Stop use and ask your doctor if symptoms persist or worsen.
- If pregnant or breast-feeding, ask a healthcare professional beofre use.

- Keep out of reach of children.

Directions

- Initially, depress pump until primed.
- Spray one dose directly into mouth.
- Ages 12 and up: 3 sprays 3 times per day.
- Ages 2-12: 2 sprays 3 times per day.

OTHER SAFETY INFORMATION

Tamper resistant for your protection. Use only if safety seal is intact.

PURPOSE

Uses for symptomatic relief of:

- intestinal upset
- bloating
- thrush
- food sensitivity
- coated tongue
- cravings
- sensitive emotions
- drowsiness
- diarrhea
- GI irritation
- flatulence